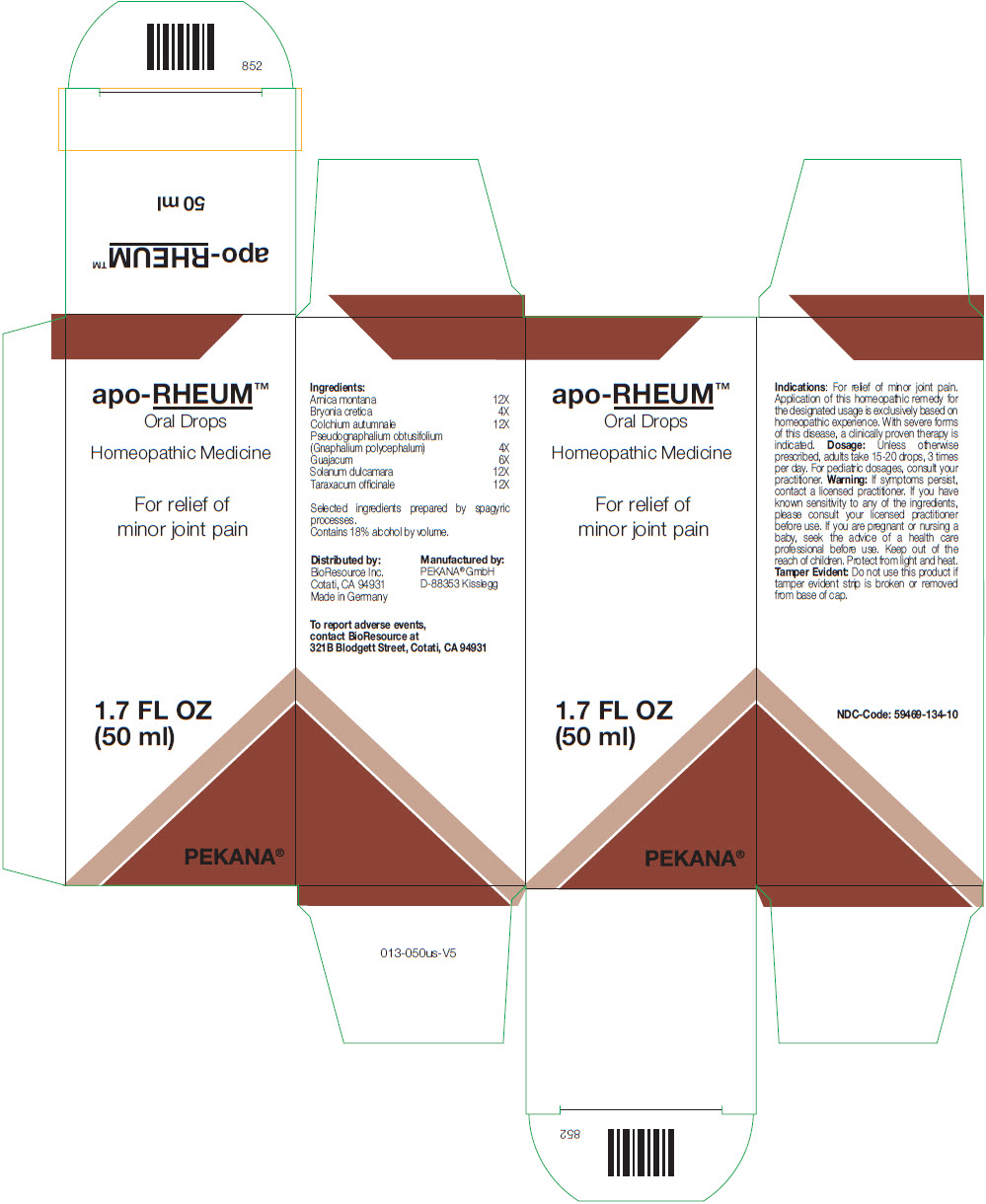 DRUG LABEL: apo-RHEUM
NDC: 59469-134 | Form: SOLUTION/ DROPS
Manufacturer: PEKANA Naturheilmittel GmbH
Category: homeopathic | Type: HUMAN OTC DRUG LABEL
Date: 20221205

ACTIVE INGREDIENTS: ARNICA MONTANA ROOT 12 [hp_X]/50 mL; BRYONIA DIOICA ROOT 4 [hp_X]/50 mL; COLCHICUM AUTUMNALE BULB 12 [hp_X]/50 mL; SOLANUM DULCAMARA TOP 12 [hp_X]/50 mL; PSEUDOGNAPHALIUM OBTUSIFOLIUM WHOLE 4 [hp_X]/50 mL; GUAIACUM OFFICINALE RESIN 6 [hp_X]/50 mL; TARAXACUM OFFICINALE WHOLE 12 [hp_X]/50 mL
INACTIVE INGREDIENTS: Water; Alcohol

apo-RHEUM™

ACTIVE INGREDIENT

Ingredients:
Arnica montana | 12X
Bryonia cretica | 4X
Colchium autumnale | 12X
Pseudognaphalium obtusifolium (Gnaphalium polycephalum) | 4X
Guajacum | 6X
Solanum dulcamara | 12X
Taraxacum officinale | 12X

Selected ingredients prepared by spagyric processes.

INACTIVE INGREDIENT

Contains 18% alcohol by volume.

Indications

PURPOSE

For relief of minor joint pain. Application of this homeopathic remedy for the designated usage is exclusively based on homeopathic experience. With severe forms of this disease, a clinically proven therapy is indicated.

Dosage

Unless otherwise prescribed, adults take 15-20 drops, 3 times per day. For pediatric dosages, consult your practitioner.

Warning

If symptoms persist, contact a licensed practitioner. If you have known sensitivity to any of the ingredients, please consult your licensed practitioner before use. If you are pregnant or nursing a baby, seek the advice of a health care professional before use.

Keep out of the reach of children.

STORAGE AND HANDLING

Protect from light and heat.

Tamper Evident

Do not use this product if tamper evident strip is broken or removed from base of cap.

QUESTIONS

To report adverse events, contact BioResource at 321B Blodgett Street, Cotati, CA 94931

Distributed by:
BioResource Inc.
Cotati, CA 94931

Manufactured by:
PEKANA® GmbH
D-88353 Kisslegg

PRINCIPAL DISPLAY PANEL - 50 ml Bottle Box

apo-RHEUM™
Oral Drops

Homeopathic Medicine

For relief of
minor joint pain

1.7 FL OZ
(50 ml)

PEKANA®